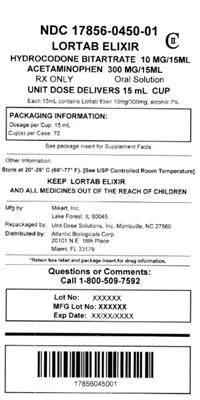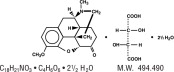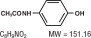 DRUG LABEL: Lortab
NDC: 17856-0450 | Form: SYRUP
Manufacturer: Atlantic Biologicals Corps
Category: prescription | Type: HUMAN PRESCRIPTION DRUG LABEL
Date: 20160629
DEA Schedule: CII

ACTIVE INGREDIENTS: Hydrocodone Bitartrate 10 mg/15 mL; Acetaminophen 300 mg/15 mL
INACTIVE INGREDIENTS: Anhydrous Citric Acid; Ethyl Maltol; Glycerin; Methylparaben; Propylene Glycol; Propylparaben; Water; Saccharin Sodium; Sorbitol; Sucrose; D&C Red No. 33; FD&C Red No. 40

DESCRIPTION

Hydrocodone bitartrate and acetaminophen is supplied in liquid form for oral administration.

(see , and). Hydrocodone bitartrate is an opioid analgesic and antitussive and occurs as fine, white crystals or as a crystalline powder. It is affected by light. The chemical name is 4,5α-epoxy-3-methoxy-17-methylmorphinan-6-one tartrate (1:1) hydrate (2:5). It has the following structural formula: WARNING: May be habit-forming PRECAUTIONS, Information for Patients/Caregivers DRUG ABUSE AND DEPENDENCE

Acetaminophen, 4'-hydroxyacetanilide, a slightly bitter, white, odorless, crystalline powder, is a non-opiate, non-salicylate analgesic and antipyretic. It has the following structural formula:

LORTAB ELIXIR (hydrocodone bitartrate and acetaminophen oral solution) contains :

 | Per | Per
 | 5 mL | 15 mL
Hydrocodone Bitartrate ...................... | 3.33 mg | 10 mg
Acetaminophen .................................. | 100 mg | 300 mg
Alcohol .............................................. | 7% | 7%

In addition, the liquid contains the following inactive ingredients: citric acid anhydrous, ethyl maltol, glycerin, methylparaben, propylene glycol, propylparaben, purified water, saccharin sodium, sorbitol solution, sucrose, with D&C Red #33 and FD&C Red #40 as coloring and natural and artificial flavoring.

CLINICAL PHARMACOLOGY

Hydrocodone is a semisynthetic narcotic analgesic and antitussive with multiple actions qualitatively similar to those of codeine. Most of these involve the central nervous system and smooth muscle. The precise mechanism of action of hydrocodone and other opiates is not known, although it is believed to relate to the existence of opiate receptors in the central nervous system. In addition to analgesia, narcotics may produce drowsiness, changes in mood and mental clouding.

The analgesic action of acetaminophen involves peripheral influences, but the specific mechanism is as yet undetermined. Antipyretic activity is mediated through hypothalamic heat regulating centers. Acetaminophen inhibits prostaglandin synthetase. Therapeutic doses of acetaminophen have negligible effects on the cardiovascular or respiratory systems; however, toxic doses may cause circulatory failure and rapid, shallow breathing.

Pharmacokinetics

The behavior of the individual components is described below.

Hydrocodone

Following a 10 mg oral dose of hydrocodone administered to five adult male subjects, the mean peak concentration was 23.6 ± 5.2 ng/mL. Maximum serum levels were achieved at 1.3 ± 0.3 hours and the half-life was determined to be 3.8 ± 0.3 hours. Hydrocodone exhibits a complex pattern of metabolism including O-demethylation, N-demethylation and 6-keto reduction to the corresponding 6-α- and 6-β hydroxymetabolites.

See for toxicity information. OVERDOSAGE

Acetaminophen

Acetaminophen is rapidly absorbed from the gastrointestinal tract and is distributed throughout most body tissues. The plasma half-life is 1.25 to 3 hours, but may be increased by liver damage and following overdosage. Elimination of acetaminophen is principally by liver metabolism (conjugation) and subsequent renal excretion of metabolites. Approximately 85% of an oral dose appears in the urine within 24 hours of administration, most as the glucuronide conjugate, with small amounts of other conjugates and unchanged drug.

See for toxicity information. OVERDOSAGE

INDICATIONS AND USAGE

LORTAB ELIXIR is indicated for the relief of moderate to moderately severe pain.

CONTRAINDICATIONS

This product should not be administered to patients who have previously exhibited hypersensitivity to hydrocodone, acetaminophen, or any other component of this product.

Patients known to be hypersensitive to other opioids may exhibit cross-sensitivity to hydrocodone.

WARNINGS

Hepatotoxicity

Acetaminophen has been associated with cases of acute liver failure, at times resulting in liver transplant and death. Most of the cases of liver injury are associated with the use of acetaminophen at doses that exceed 4000 milligrams per day, and often involve more than one acetaminophen-containing product. The excessive intake of acetaminophen may be intentional to cause self-harm or unintentional as patients attempt to obtain more pain relief or unknowingly take other acetaminophen-containing products.

The risk of acute liver failure is higher in individuals with underlying liver disease and in individuals who ingest alcohol while taking acetaminophen.

Instruct patients to look for acetaminophen or APAP on package labels and not to use more than one product that contains acetaminophen. Instruct patients to seek medical attention immediately upon ingestion of more than 4000 milligrams of acetaminophen per day, even if they feel well.

Serious Skin Reactions

Rarely, acetaminophen may cause serious skin reactions such as acute generalized exanthematous pustulosis (AGEP), Stevens-Johnson Syndrome (SJS), and toxic epidermal necrolysis (TEN), which can be fatal. Patients should be informed about the signs of serious skin reactions, and use of the drug should be discontinued at the first appearance of skin rash or any other sign of hypersensitivity.

Hypersensitivity/anaphylaxis

There have been post-marketing reports of hypersensitivity and anaphylaxis associated with use of acetaminophen. Clinical signs included swelling of the face, mouth, and throat, respiratory distress, urticaria, rash, pruritus, and vomiting. There were infrequent reports of life-threatening anaphylaxis requiring emergency medical attention. Instruct patients to discontinue LORTAB ELIXIR immediately and seek medical care if they experience these symptoms. Do not prescribe LORTAB ELIXIR for patients with acetaminophen allergy.

Respiratory Depression

At high doses or in sensitive patients, hydrocodone may produce dose-related respiratory depression by acting directly on the brain stem respiratory center. Hydrocodone also affects the center that controls respiratory rhythm, and may produce irregular and periodic breathing.

Infants may have increased sensitivity to the respiratory depressant effects of opioids (see). If use of LORTAB ELIXIR in such patients is contemplated, it should be administered cautiously, in substantially reduced initial doses, by personnel experienced in administering opioids to infants, and with intensive monitoring. PRECAUTIONS, Pediatric Use

Head Injury and Increased Intracranial Pressure

The respiratory depressant effects of narcotics and their capacity to elevate cerebrospinal fluid pressure may be markedly exaggerated in the presence of head injury, other intracranial lesions or a preexisting increase in intracranial pressure. Furthermore, narcotics produce adverse reactions, which may obscure the clinical course of patients with head injuries.

Acute Abdominal Conditions

The administration of narcotics may obscure the diagnosis or clinical course of patients with acute abdominal conditions.

Misuse Abuse and Diversion of Opioids

LORTAB ELIXIR contains hydrocodone, an opioid agonist, and is a Schedule II controlled substance. Opioid agonists have the potential for being abused and are sought by abusers and people with addiction disorders, and are subject to diversion.

LORTAB ELIXIR can be abused in a manner similar to other opioid agonists, legal or illicit. This should be considered when prescribing or dispensing LORTAB ELIXIR in situations where the physician or pharmacist is concerned about an increased risk of misuse, abuse or diversion (see). DRUG ABUSE AND DEPENDENCE

PRECAUTIONS

General

Special Risk Patients

As with any narcotic analgesic agent, LORTAB ELIXIR should be used with caution in elderly or debilitated patients, and those with severe impairment of hepatic or renal function, hypothyroidism, Addison's disease, prostatic hypertrophy or urethral stricture. The usual precautions should be observed and the possibility of respiratory depression should be kept in mind.

Cough Reflex

Hydrocodone suppresses the cough reflex; as with all narcotics, caution should be exercised when LORTAB ELIXIR is used postoperatively and in patients with pulmonary disease.

Information for Patients/Caregivers

- Do not take LORTAB ELIXIR if you are allergic to any of its ingredients.
- If you develop signs of allergy such as a rash or difficulty breathing, stop taking LORTAB ELIXIR and contact your healthcare provider immediately.
- Do not take more than 4000 milligrams of acetaminophen per day. Call your doctor if you took more than the recommended dose.

Hydrocodone, like all narcotics, may impair mental and/or physical abilities required for the performance of potentially hazardous tasks such as driving a car or operating machinery. Such tasks should be avoided while taking this product.

Alcohol and other CNS depressants may produce an additive CNS depression, when taken with this combination product, and should be avoided.

Hydrocodone may be habit-forming. Patients should take the drug only for as long as it is prescribed, in the amounts prescribed, and no more frequently than prescribed.

Physicians should instruct patients and caregivers to read the patient information leaflet, which appears as the last section of the labeling.

Laboratory Tests

In patients with severe hepatic or renal disease, effects of therapy should be monitored with serial liver and/or renal function tests.

Drug Interactions

Patients receiving narcotics, antihistamines, antipsychotics, antianxiety agents, or other CNS depressants (including alcohol) concomitantly with LORTAB ELIXIR may exhibit an additive CNS depression. When combined therapy is contemplated, the dose of one or both agents should be reduced.

The use of MAO inhibitors or tricyclic antidepressants with hydrocodone preparations may increase the effect of either the antidepressant or hydrocodone.

Drug/Laboratory Test Interactions

Acetaminophen may produce false-positive test results for urinary 5-hydroxyindoleacetic acid.

Carcinogenesis, Mutagenesis, Impairment of Fertility

No adequate studies have been conducted in animals to determine whether hydrocodone has a potential for carcinogenesis, mutagenesis, or impairment of fertility.

Hydrocodone has not demonstrated mutagenic potential using the Ames Salmonella-Microsomal Activation test, the Basc test on Drosophila germ cells, and the Micronucleus test on mouse bone marrow.

No adequate studies have been conducted in animals to determine whether acetaminophen has a potential for carcinogenesis, mutagenesis, or impairment of fertility.

Acetaminophen has not demonstrated mutagenic potential using the Ames Salmonella-Microsomal Activation test, the Basc test on Drosophila germ cells, and the Micronucleus test on mouse bone marrow.

Pregnancy

Teratogenic Effects:

Pregnancy Category C

There are no adequate and well-controlled studies in pregnant women. LORTAB ELIXIR should be used during pregnancy only if the potential benefit justifies the potential risk to the fetus.

Nonteratogenic Effects

Babies born to mothers who have been taking opioids regularly prior to delivery will be physically dependent. The withdrawal signs include irritability and excessive crying, tremors, hyperactive reflexes, increased respiratory rate, increased stools, sneezing, yawning, vomiting and fever. These signs usually appear during the first few days of life. The intensity of the syndrome does not always correlate with the duration of maternal opioid use or dose. There is no consensus on the best method of managing withdrawal.

Labor and Delivery

Narcotic analgesics cross the placental barrier. The closer to delivery and the larger the dose used, the greater the possibility of respiratory depression in the newborn. Narcotic analgesics should be avoided during labor if delivery of a premature infant is anticipated. If the mother has received narcotic analgesics during labor, newborn infants should be observed closely for signs of respiratory depression. Resuscitation may be required (see). The effect of hydrocodone, if any, on the later growth, development, and functional maturation of the child is unknown. OVERDOSAGE

Nursing Mothers

Acetaminophen is excreted in breast milk in small amounts, but the significance of its effects on nursing infants is not known. It is not known whether hydrocodone is excreted in human milk. Because many drugs are excreted in human milk and because of the potential for serious adverse reactions in nursing infants from hydrocodone and acetaminophen, a decision should be made whether to discontinue nursing or to discontinue the drug, taking into account the importance of the drug to the mother.

Pediatric Use

Safety and effectiveness in the pediatric population below the age of two years have not been established. Use of LORTAB ELIXIR in the pediatric population is supported by the evidence from adequate and well controlled studies of hydrocodone and acetaminophen combination products in adults with additional data which support the development of metabolic pathways in children two years of age and over (see for pediatric dosage information). DOSAGE AND ADMINISTRATION

Geriatric Use

Clinical studies of hydrocodone bitartrate and acetaminophen oral solution did not include sufficient numbers of subjects aged 65 and over to determine whether they respond differently from younger subjects. Other reported clinical experience has not identified differences in responses between the elderly and younger patients. In general, dose selection for an elderly patient should be cautious, usually starting at the low end of the dosing range, reflecting the greater frequency of decreased hepatic, renal, or cardiac function, and of concomitant disease or other drug therapy.

Hydrocodone and the major metabolites of acetaminophen are known to be substantially excreted by the kidney. Thus the risk of toxic reactions may be greater in patients with impaired renal function due to the accumulation of the parent compound and/or metabolites in the plasma. Because elderly patients are more likely to have decreased renal function, care should be taken in dose selection, and it may be useful to monitor renal function.

Hydrocodone may cause confusion and over-sedation in the elderly; elderly patients generally should be started on low doses of LORTAB ELIXIR and observed closely.

ADVERSE REACTIONS

Potential effects of high dosage are also listed in the OVERDOSAGE section.

Bradycardia, cardiac arrest, circulatory collapse, renal toxicity, renal tubular necrosis, hypotension. Cardio-renal:

Anxiety, dizziness, drowsiness, dysphoria, euphoria, fear, general malaise, impairment of mental and physical performance, lethargy, light-headedness, mental clouding, mood changes, psychological dependence, sedation, somnolence progressing to stupor or coma. Central Nervous System/Psychiatric:

Hypoglycemic coma. Endocrine:

Abdominal pain, constipation, gastric distress, heartburn, hepatic necrosis, hepatitis, occult blood loss, nausea, peptic ulcer, and vomiting. Gastrointestinal System:

Spasm of vesical sphincters, ureteral spasm, and urinary retention. Genitourinary System:

Agranulocytosis, hemolytic anemia, iron deficiency anemia, prolonged bleeding time, thrombocytopenia. Hematologic:

Allergic reactions. Hypersensitivity:

Skeletal muscle flaccidity. Musculoskeletal:

Acute airway obstruction, apnea, dose-related respiratory depression (see), shortness of breath. Respiratory Depression: OVERDOSAGE

Cases of hearing impairment or permanent loss have been reported predominantly in patients with chronic overdose. Special Senses:

Cold and clammy skin, diaphoresis, pruritus, rash. Skin:

DRUG ABUSE AND DEPENDENCE

Misuse Abuse and Diversion of Opioids

LORTAB ELIXIR contains hydrocodone, an opioid agonist, and is a Schedule II controlled substance. LORTAB ELIXIR, and other opioids used in analgesia can be abused and are subject to criminal diversion.

Addiction is a primary, chronic, neurobiologic disease, with genetic psychosocial, and environmental factors influencing its development and manifestations. It is characterized by behaviors that include one or more of the following: impaired control over drug use, compulsive use, continued use despite harm, and craving. Drug addiction is a treatable disease utilizing a multidisciplinary approach, but relapse is common.

“Drug seeking” behavior is very common in addicts and drug abusers. Drug seeking tactics include emergency calls or visits near the end of office hours, refusal to undergo appropriate examination, testing or referral, repeated “loss” of prescriptions, tampering with prescriptions and reluctance to provide prior medical records or contact information for other treating physician(s). “Doctor shopping” to obtain additional prescriptions is common among drug abusers and people suffering from untreated addiction.

Abuse and addiction are separate and distinct from physical dependence and tolerance. Physical dependence usually assumes clinically significant dimensions only after several weeks of continued opioid use, although a mild degree of physical dependence may develop after a few days of opioid therapy. Tolerance, in which increasingly large doses are required in order to produce the same degree of analgesia, is manifested initially by a shortened duration of analgesic effect, and subsequently by decreases in the intensity of analgesia. The rate of development of tolerance varies among patients. Physicians should be aware that abuse of opioids can occur in the absence of true addiction and is characterized by misuse for non-medical purposes, often in combination with other psychoactive substances. LORTAB ELIXIR, like other opioids, may be diverted for non-medical use. Record-keeping of prescribing information, including quantity, frequency, and renewal requests is strongly advised.

Proper assessment of the patient, proper prescribing practices, periodic re-evaluation of therapy, and proper dispensing and storage are appropriate measures that help to limit abuse of opioid drugs.

OVERDOSAGE

Following an acute overdosage, toxicity may result from hydrocodone or acetaminophen.

Signs and Symptoms

: Serious overdose with hydrocodone is characterized by respiratory depression (a decrease in respiratory rate and/or tidal volume, Cheyne-Stokes respiration, cyanosis), extreme somnolence progressing to stupor or coma, skeletal muscle flaccidity, cold and clammy skin, and sometimes bradycardia and hypotension. In severe overdosage, apnea, circulatory collapse, cardiac arrest and death may occur. Hydrocodone

: In acetaminophen overdosage: dose-dependent, potentially fatal hepatic necrosis is the most serious adverse effect. Renal tubular necrosis, hypoglycemic coma and coagulation defects may also occur. Early symptoms following a potentially hepatotoxic overdose may include: nausea, vomiting, diaphoresis and general malaise. Clinical and laboratory evidence of hepatic toxicity may not be apparent until 48 to 72 hours post-ingestion. Acetaminophen

Treatment

A single or multiple drug overdose with hydrocodone and acetaminophen is a potentially lethal polydrug overdose, and consultation with a regional poison control center is recommended. Immediate treatment includes support of cardiorespiratory function and measures to reduce drug absorption. Oxygen, intravenous fluids, vasopressors, and other supportive measures should be employed as indicated. Assisted or controlled ventilation should also be considered.

For hydrocodone overdose, primary attention should be given to the reestablishment of adequate respiratory exchange through provision of a patent airway and the institution of assisted or controlled ventilation. The narcotic antagonist naloxone hydrochloride is a specific antidote against respiratory depression which may result from overdosage or unusual sensitivity to narcotics, including hydrocodone. Since the duration of action of hydrocodone may exceed that of the antagonist, the patient should be kept under continued surveillance, and repeated doses of the antagonist should be administered as needed to maintain adequate respiration. A narcotic antagonist should not be administered in the absence of clinically significant respiratory or cardiovascular depression.

Gastric decontamination with activated charcoal should be administered just prior to N-acetylcysteine (NAC) to decrease systemic absorption if acetaminophen ingestion is known or suspected to have occurred within a few hours of presentation. Serum acetaminophen levels should be obtained immediately if the patient presents 4 hours or more after ingestion to assess potential risk of hepatotoxicity; acetaminophen levels drawn less than 4 hours post-ingestion may be misleading. To obtain the best possible outcome, NAC should be administered as soon as possible where impending or evolving liver injury is suspected. Intravenous NAC may be administered when circumstances preclude oral administration.

Vigorous supportive therapy is required in severe intoxication. Procedures to limit the continuing absorption of the drug must be readily performed since the hepatic injury is dose dependent and occurs early in the course of intoxication.

DOSAGE AND ADMINISTRATION

Dosage should be adjusted according to severity of the pain and the response of the patient. However, it should be kept in mind that tolerance to hydrocodone can develop with continued use and that the incidence of untoward effects is dose related.

The usual adult dosage is 11.25 milliliters every 4 to 6 hours as needed for pain. The total daily dosage for adults should not exceed 67.5 milliliters.

The usual dosages for children are given by the table below, and are to be given every 4 to 6 hours as needed for pain. These dosages correspond to an average individual dose of 0.20 mL/kg of LORTAB ELIXIR (providing 0.135 mg/kg of hydrocodone bitartrate and 4.0 mg/kg of acetaminophen). Dosing should be based on weight whenever possible.

BODY WEIGHT | APPROXIMATE AGE | DOSE every 4 to 6 hours | MAXIMUM TOTAL DAILY DOSE (6 doses per day)
12 to 15 kg (27 to 34 lbs.) | 2 to 3 years | 2.8 mL | 16.8 mL
16 to 22 kg (35 to 50 lbs.) | 4 to 6 years | 3.75 mL | 22.5 mL
23 to 31 kg (51 to 69 lbs.) | 7 to 9 years | 5.6 mL | 33.6 mL
32 to 45 kg (70 to 100 lbs.) | 10 to 13 years | 7.5 mL | 45 mL
46 kg and up (101 lbs. and up) | 14 years to adult | 11.25 mL | 67.5 mL

The total daily dosage for children should not exceed 6 doses per day.

It is of utmost importance that the dose of LORTAB ELIXIR be administered accurately. It is strongly recommended that care givers obtain and use a calibrated measuring device. Health care providers should recommend a dropper that can measure and deliver the prescribed dose accurately, and instruct care givers to use extreme caution in measuring the dosage.

HOW SUPPLIED

NDC:17856-0450-1 15 mL in a CUP, UNIT-DOSE

STORAGE AND HANDLING

Store at 20° to 25°C (68° to 77°F) [see USP Controlled Room Temperature]. STORAGE:

Dispense in a tight, light-resistant container with a child-resistant closure. PHARMACIST:

A Schedule CII Narcotic.

Manufactured for Lake Forest, IL 60045 Manufactured by Atlanta, GA 30318
Akorn, Inc.
Mikart Inc.

Patient Information Leaflet LORTAB
® ELIXIR CII (hydrocodone bitartrate and acetaminophen oral solution) 10 mg/300 mg per 15 mL Rx only

LORTAB (pronounced LOR-tab) ELIXIR is used to relieve moderate to moderately severe pain. You should not take LORTAB ELIXIR if you are allergic to hydrocodone or acetaminophen. The most common side effects of LORTAB ELIXIR are abdominal pain, dizziness, drowsiness, light-headedness, nausea, shortness of breath, unusual tiredness, and vomiting. Take this medicine as directed by your doctor. Do not take more of it, do not take it more often, and do not take it for a longer time than your doctor ordered. Summary

Uses

LORTAB ELIXIR is an analgesic used to relieve moderate to moderately severe pain. LORTAB ELIXIR is a combination product containing hydrocodone (hye-droe-KO-done) bitartrate and acetaminophen (a seat-a-MIN-oh-fen). Hydrocodone is a narcotic pain reliever and a cough suppressant. Acetaminophen is a non-narcotic pain reliever and fever reducer. A narcotic analgesic and acetaminophen used together may provide better pain relief than either product used alone. If you have any questions, please call your doctor or pharmacist.

General Cautions

- Do not take this drug if you have allergies or unusual reactions to narcotic pain relievers or acetaminophen because it is likely that you may also be allergic to LORTAB ELIXIR.
- This product may inhibit your mental and physical abilities required for the performance of potentially hazardous tasks such as driving a car or operating machinery. Such tasks should be avoided while you are taking this product.
- This medicine may not be right for you. Check with your doctor or pharmacist, if you:
  - are pregnant.
  - are nursing.
  - are taking other medications: narcotic pain relievers; allergy medicines; antidepressant medicines; acetaminophen-containing medicines or other medicines that cause central nervous system depression, including alcohol.
  - have other medical problems: a history of drug or alcohol abuse; recent head injury; emphysema, asthma, or other chronic lung disease; liver disease, kidney disease; underactive thyroid, Addison's disease, enlarged prostate or difficulty urinating.

Proper Use

Take this medicine as directed by your doctor. Do not share it with anyone else. This medicine can cause drug dependence and has the potential for abuse. Do not take more of it, do not take it more often, and do not take it for a longer time than your doctor ordered. If you think that this medicine is not working properly after taking it for some time, do not increase the dose. Check with your doctor or pharmacist.

Dosing

The dose of this medication will be different for different patients. Follow the directions provided by your doctor. The following information includes only the average doses of this medication. . If your dose is different, do not change doses unless your doctor tells you to do so

BODY WEIGHT | APPROXIMATE AGE | DOSE every 4 to 6 hours | MAXIMUM TOTAL DAILY DOSE (6 doses per day)
12 to 15 kg (27 to 34 lbs.) | 2 to 3 years | 2.8 mL | 16.8 mL
16 to 22 kg (35 to 50 lbs.) | 4 to 6 years | 3.75 mL | 22.5 mL
23 to 31 kg (51 to 69 lbs.) | 7 to 9 years | 5.6 mL | 33.6 mL
32 to 45 kg (70 to 100 lbs.) | 10 to 13 years | 7.5 mL | 45 mL
46 kg and up (101 lbs. and up) | 14 years to adult | 11.25 mL | 67.5 mL

It is very important that LORTAB ELIXIR be dosed accurately. It is strongly recommended that you obtain and use a proper measuring device. Ask your doctor or pharmacist for help to find a dropper that can measure the needed dose properly and ask for help if you do not understand how to use the dropper.

Missed Dose

- To avoid a possible overdose, it is important that you do not take more than a single dosage at one time, or that you don't take doses at intervals less than 4 hours apart.
- If you miss taking a dose of LORTAB ELIXIR, take it as soon as you remember. However, make sure to wait at least 4 hours before taking your next dose.
- If you missed taking a dose, and it is almost time for your next dose, skip the missed dose and take your medicine as scheduled.
- Do not double the prescribed dose.

Possible Side Effects

Side effects you may experience include abdominal pain, constipation, difficulty urinating, dizziness, drowsiness, fear, fuzzy thinking, general feeling of discomfort or illness, light-headedness, mood changes, nausea, nervousness, rash, shortness of breath, slower reactions, unusual tiredness, and vomiting.

Call your doctor if these effects continue or are bothersome.

Side effects not listed above may sometimes occur. If you notice any other effects, check with your doctor.

Storage

- Keep out of reach of children.
- Store at room temperature (protect from heat, do not refrigerate).
- Keep in original labeled bottle.
- Discard medicines that are old or no longer needed.
- Even a single overdose of this medicine may be a life-threatening situation. If you suspect that you or someone else may have taken more than the prescribed dose of this medicine, contact your local poison control center or emergency room immediately. This medicine was prescribed for your particular condition. Do not use it for another condition or give the drug to others.
- This leaflet provides a summary of information about LORTAB ELIXIR. If you have any question or concerns, or want more information about LORTAB ELIXIR, contact your doctor or pharmacist. Your pharmacist also has a longer leaflet about LORTAB ELIXIR that is written for health professionals that you can ask to read.

Prepared by: LO00N Code 1059D00 Rev. 01/15 Akorn, Inc.

Patient Information Leaflet LORTAB
® ELIXIR CII (hydrocodone bitartrate and acetaminophen oral solution) 10 mg/300 mg per 15 mL Rx only

LORTAB (pronounced LOR-tab) ELIXIR is used to relieve moderate to moderately severe pain. You should not take LORTAB ELIXIR if you are allergic to hydrocodone or acetaminophen. The most common side effects of LORTAB ELIXIR are abdominal pain, dizziness, drowsiness, light-headedness, nausea, shortness of breath, unusual tiredness, and vomiting. Take this medicine as directed by your doctor. Do not take more of it, do not take it more often, and do not take it for a longer time than your doctor ordered. Summary

Uses

LORTAB ELIXIR is an analgesic used to relieve moderate to moderately severe pain. LORTAB ELIXIR is a combination product containing hydrocodone (hye-droe-KO-done) bitartrate and acetaminophen (a seat-a-MIN-oh-fen). Hydrocodone is a narcotic pain reliever and a cough suppressant. Acetaminophen is a non-narcotic pain reliever and fever reducer. A narcotic analgesic and acetaminophen used together may provide better pain relief than either product used alone. If you have any questions, please call your doctor or pharmacist.

General Cautions

- Do not take this drug if you have allergies or unusual reactions to narcotic pain relievers or acetaminophen because it is likely that you may also be allergic to LORTAB ELIXIR.
- This product may inhibit your mental and physical abilities required for the performance of potentially hazardous tasks such as driving a car or operating machinery. Such tasks should be avoided while you are taking this product.
- This medicine may not be right for you. Check with your doctor or pharmacist, if you:
  - are pregnant.
  - are nursing.
  - are taking other medications: narcotic pain relievers; allergy medicines; antidepressant medicines; acetaminophen-containing medicines or other medicines that cause central nervous system depression, including alcohol.
  - have other medical problems: a history of drug or alcohol abuse; recent head injury; emphysema, asthma, or other chronic lung disease; liver disease, kidney disease; underactive thyroid, Addison's disease, enlarged prostate or difficulty urinating.

Proper Use

Take this medicine as directed by your doctor. Do not share it with anyone else. This medicine can cause drug dependence and has the potential for abuse. Do not take more of it, do not take it more often, and do not take it for a longer time than your doctor ordered. If you think that this medicine is not working properly after taking it for some time, do not increase the dose. Check with your doctor or pharmacist.

Dosing

The dose of this medication will be different for different patients. Follow the directions provided by your doctor. The following information includes only the average doses of this medication. . If your dose is different, do not change doses unless your doctor tells you to do so

BODY WEIGHT | APPROXIMATE AGE | DOSE every 4 to 6 hours | MAXIMUM TOTAL DAILY DOSE (6 doses per day)
12 to 15 kg (27 to 34 lbs.) | 2 to 3 years | 2.8 mL | 16.8 mL
16 to 22 kg (35 to 50 lbs.) | 4 to 6 years | 3.75 mL | 22.5 mL
23 to 31 kg (51 to 69 lbs.) | 7 to 9 years | 5.6 mL | 33.6 mL
32 to 45 kg (70 to 100 lbs.) | 10 to 13 years | 7.5 mL | 45 mL
46 kg and up (101 lbs. and up) | 14 years to adult | 11.25 mL | 67.5 mL

It is very important that LORTAB ELIXIR be dosed accurately. It is strongly recommended that you obtain and use a proper measuring device. Ask your doctor or pharmacist for help to find a dropper that can measure the needed dose properly and ask for help if you do not understand how to use the dropper.

Missed Dose

- To avoid a possible overdose, it is important that you do not take more than a single dosage at one time, or that you don't take doses at intervals less than 4 hours apart.
- If you miss taking a dose of LORTAB ELIXIR, take it as soon as you remember. However, make sure to wait at least 4 hours before taking your next dose.
- If you missed taking a dose, and it is almost time for your next dose, skip the missed dose and take your medicine as scheduled.
- Do not double the prescribed dose.

Possible Side Effects

Side effects you may experience include abdominal pain, constipation, difficulty urinating, dizziness, drowsiness, fear, fuzzy thinking, general feeling of discomfort or illness, light-headedness, mood changes, nausea, nervousness, rash, shortness of breath, slower reactions, unusual tiredness, and vomiting.

Call your doctor if these effects continue or are bothersome.

Side effects not listed above may sometimes occur. If you notice any other effects, check with your doctor.

Storage

- Keep out of reach of children.
- Store at room temperature (protect from heat, do not refrigerate).
- Keep in original labeled bottle.
- Discard medicines that are old or no longer needed.
- Even a single overdose of this medicine may be a life-threatening situation. If you suspect that you or someone else may have taken more than the prescribed dose of this medicine, contact your local poison control center or emergency room immediately. This medicine was prescribed for your particular condition. Do not use it for another condition or give the drug to others.
- This leaflet provides a summary of information about LORTAB ELIXIR. If you have any question or concerns, or want more information about LORTAB ELIXIR, contact your doctor or pharmacist. Your pharmacist also has a longer leaflet about LORTAB ELIXIR that is written for health professionals that you can ask to read.

Prepared by: Code 1059D00-P Rev. 01/15 Akorn, Inc.